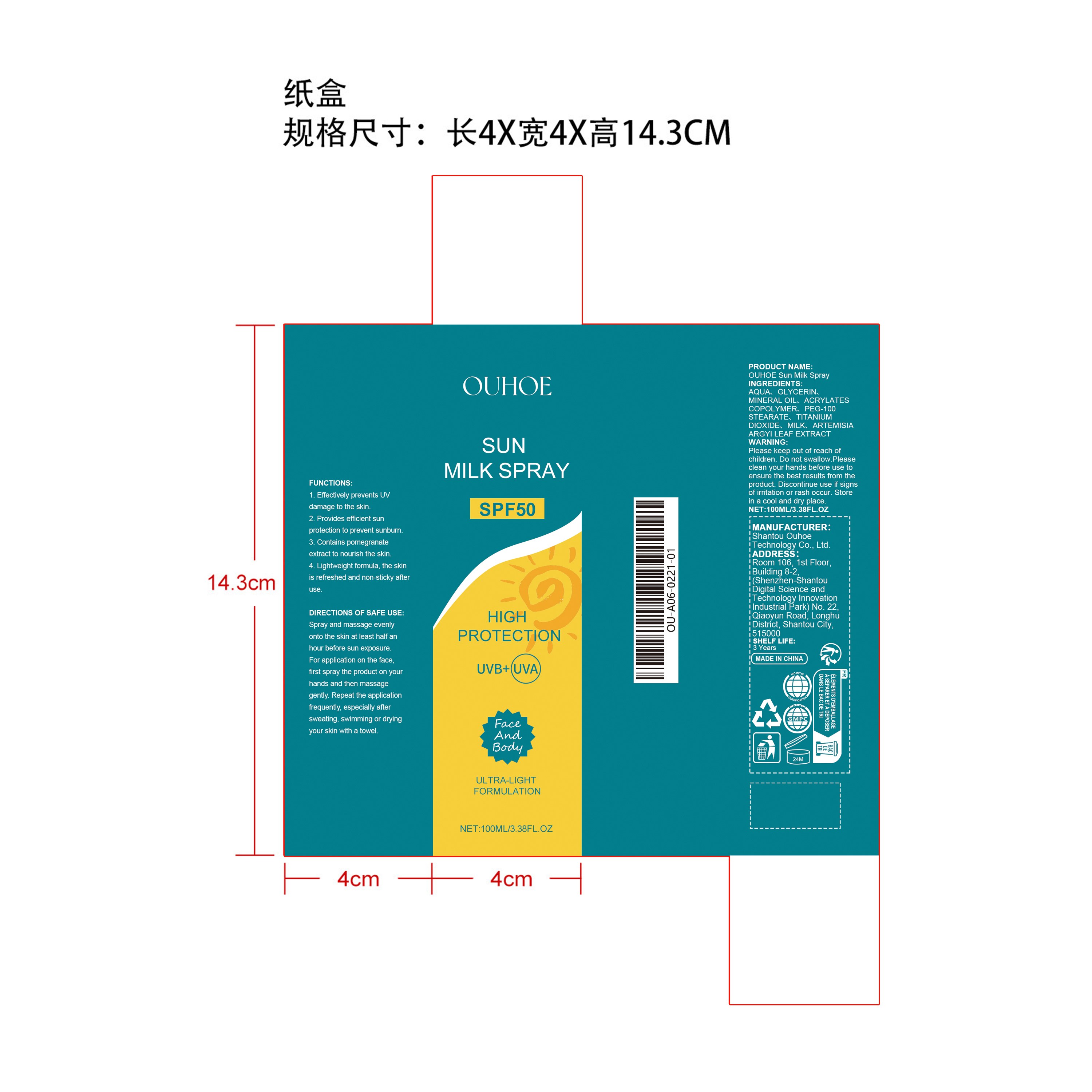 DRUG LABEL: OUHOE Sun Milk
NDC: 85163-020 | Form: SPRAY
Manufacturer: Shantou Ouhoe Technology Co., Ltd.
Category: otc | Type: HUMAN OTC DRUG LABEL
Date: 20251226

ACTIVE INGREDIENTS: ARTEMISIA ARGYI LEAF 0.01 mg/100 mg
INACTIVE INGREDIENTS: MINERAL OIL 3 mg/100 mg; ACRYLATES CROSSPOLYMER-4 2 mg/100 mg; MILK 0.1 mg/100 mg; PEG-100 STEARATE 2 mg/100 mg; AQUA 89.69 mg/100 mg; TITANIUM DIOXIDE 0.2 mg/100 mg; GLYCERIN 3 mg/100 mg

ACTIVE INGREDIENT

ARTEMISIA ARGYI LEAF EXTRACT

PURPOSE

1. Effectively prevents UV damage to the skin.

2. Provides efficient sun protection to prevent sunburn.

3. Contains pomegranate extract to nourish the skin.

4. Lightweight formula, the skin is refreshed and non-sticky after use.

WHEN USING

Spray and massage evenly onto the skin at least half an hour before sun exposure. For application on the face, first spray the product on your hands and then massage gently. Repeat the application frequently, especially after sweating, swimming or drying your skin with a towel.

WARNINGS

Please keep out of reach of children. Do not swallow.Please clean your hands before use to ensure the best results from the product. Discontinue use if signs of irritation or rash occur. Store in a cool and dry place.

DO NOT USE

Discontinue use if signs of irritation or rash occur.

STOP USE

Discontinue use if signs of irritation or rash occur.

KEEP OUT OF REACH OF CHILDREN

Please keep out of reach of children. Do not swallow.

STORAGE AND HANDLING

Store in a cool and dry place.

INACTIVE INGREDIENT

AQUA、GLYCERIN、MINERAL OIL、ACRYLATES COPOLYMER、PEG-100 STEARATE、TITANIUM DIOXIDE、MILK

INDICATIONS AND USAGE

Spray and massage evenly onto the skin at least half an hour before sun exposure. For application on the face, first spray the product on your hands and then massage gently. Repeat the application frequently, especially after sweating, swimming or drying your skin with a towel.

DOSAGE AND ADMINISTRATION

Spray and massage evenly onto the skin at least half an hour before sun exposure. For application on the face, first spray the product on your hands and then massage gently. Repeat the application frequently, especially after sweating, swimming or drying your skin with a towel.